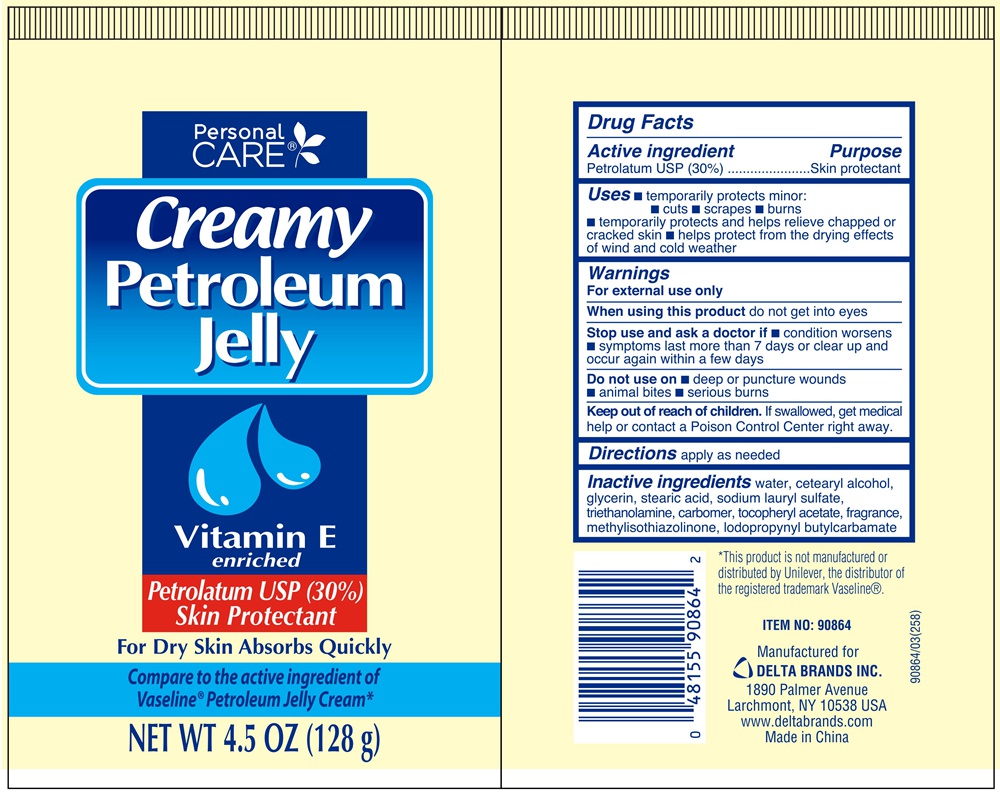 DRUG LABEL: PERSONAL CARE CREAMY PETROLEUM
NDC: 76176-022 | Form: JELLY
Manufacturer: Ningbo Liyuan Daily Chemical Products Co.,Ltd.
Category: otc | Type: HUMAN OTC DRUG LABEL
Date: 20240101

ACTIVE INGREDIENTS: PETROLATUM 30 g/100 g
INACTIVE INGREDIENTS: ALPHA-TOCOPHEROL ACETATE; SODIUM LAURYL SULFATE; STEARIC ACID; IODOPROPYNYL BUTYLCARBAMATE; METHYLISOTHIAZOLINONE; CARBOMER 940; CETYL ALCOHOL; WATER; GLYCERIN

Drug Facts Active ingredient

Petrolatum 30%

Purpose

Skin protectant

Uses

- temporarily protects minor: cuts, scrapes, burns.
- temporarily protects and helps relieve chapped or cracked skin.
- helps protect from the drying effects of wind and cold weather.

Warnings

For external use only.

When using this product do not get into eyes.

Stop use and ask a doctor if condition worsens, symptoms last more than 7 days or clear up and occur again within a few days.

Do not use on deep or puncture wounds, animal bites, serious burns.

Keep out of reach of children.

If swallowed, get medical help or contact a Poison Control Center right away.

Directions

apply as needed.

Inactive ingredients

water, cetearyl alcohol, glycerin, stearic acid, sodium lauryl sulfate, triethanolamine, carbomer, tocopheryl acetate, fragrance, methylisothiazolinone, iodopropynyl butylcarbamate